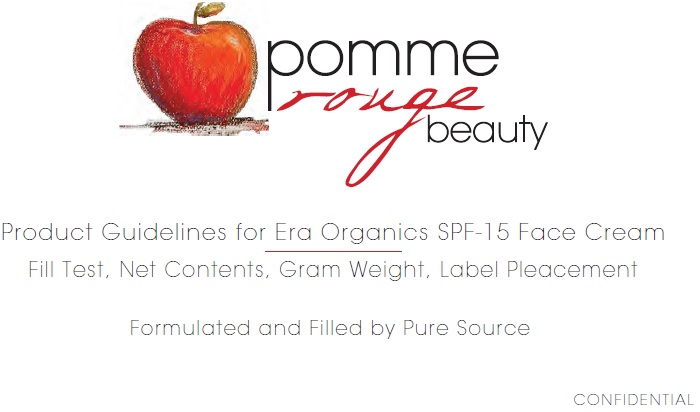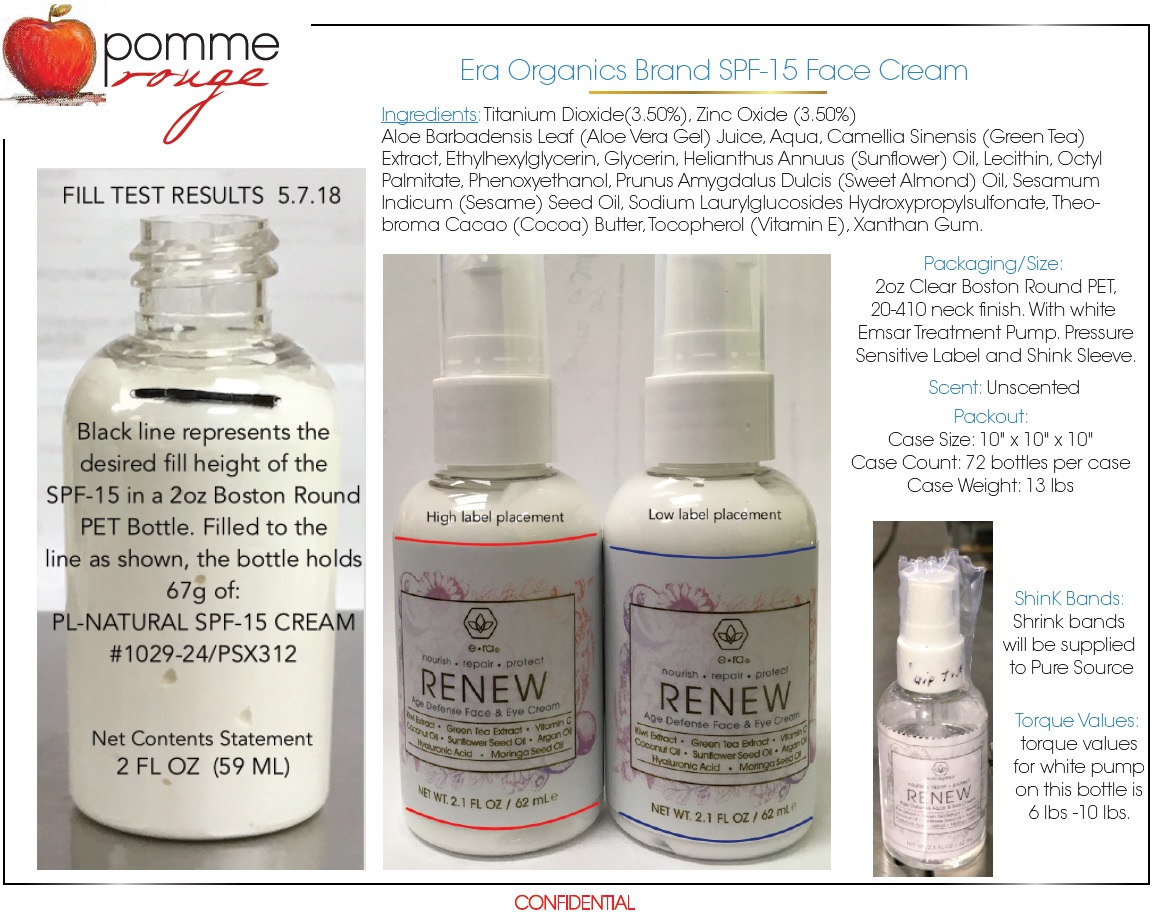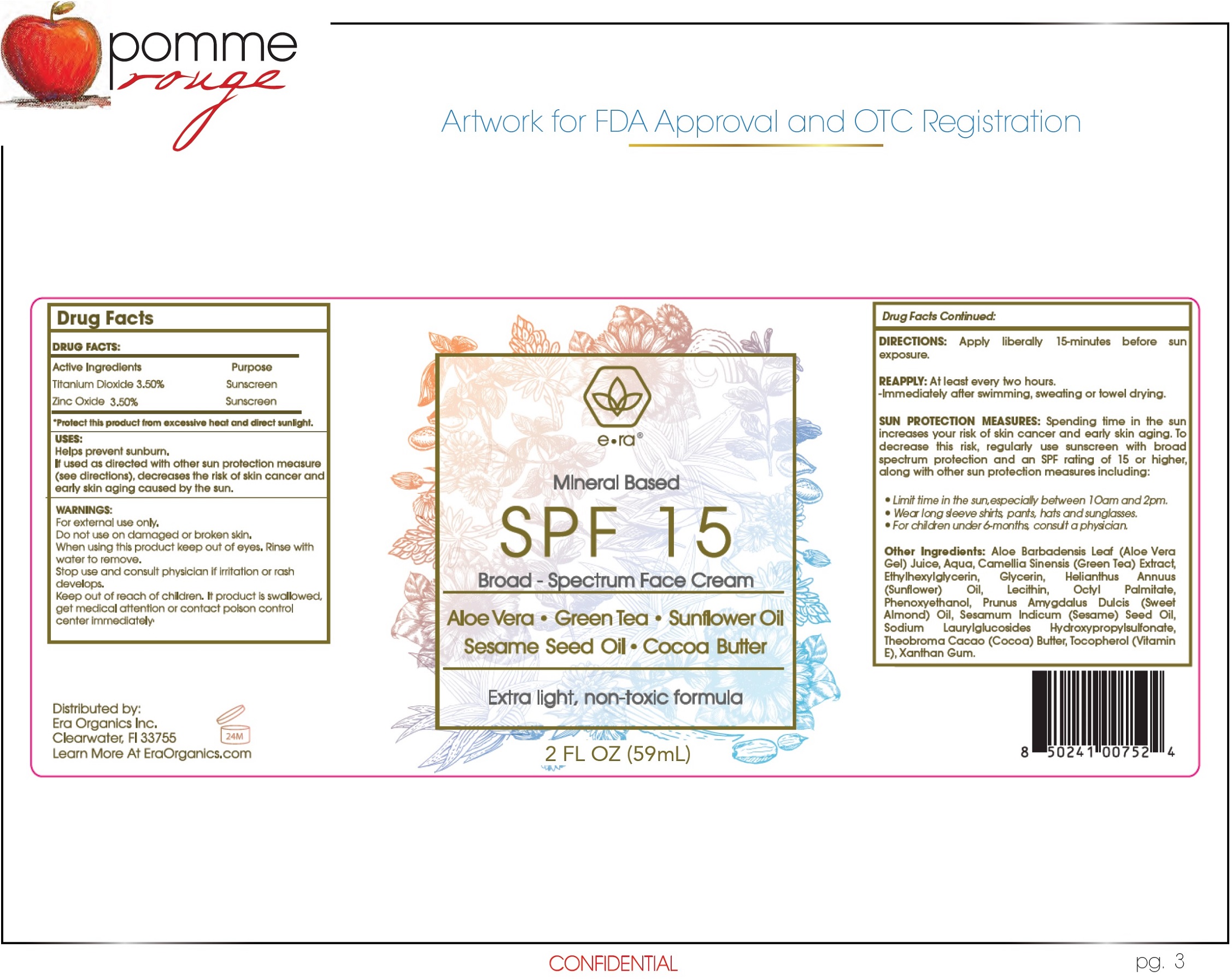 DRUG LABEL: Era Organics Mineral Based SPF 15
NDC: 72400-752 | Form: CREAM
Manufacturer: Era Organics, Inc.
Category: otc | Type: HUMAN OTC DRUG LABEL
Date: 20180730

ACTIVE INGREDIENTS: TITANIUM DIOXIDE 35 mg/1 mL; ZINC OXIDE 35 mg/1 mL
INACTIVE INGREDIENTS: ALOE VERA LEAF; WATER; GREEN TEA LEAF; ETHYLHEXYLGLYCERIN; GLYCERIN; ETHYLHEXYL PALMITATE; PHENOXYETHANOL; ALMOND OIL; SESAME OIL; COCOA; TOCOPHEROL; XANTHAN GUM

Era Organics Mineral Based SPF 15

Active Ingredients

Titanium Dioxide 3.50%

Zinc Oxide 3.50%

Purpose

Sunscreen

*Protect this product from excessive heat and direct sunlight.

USES:

Helps prevent sunburn.

If used as directed with other sun protection measure (see directions), decreases the risk of skin cancer and early skin aging caused by the sun.

WARNINGS:

For external use only.

Do not use

on damaged or broken skin.

When using this product

keep out of eyes. Rinse with water to remove.

Stop use and consult physician

if irritation or rash develops.

Keep out of reach of children.

If product is swallowed, get medical attention or contact poison control center immediately

DIRECTIONS:

Apply liberally 15-minutes before sun exposure.

REAPPLY: At least every two hours.

- Immediately after swimming, sweating or towel drying.

SUN PROTECTION MEASURES: Spending time in the sun increases your risk of skin cancer and early skin aging. to decrease this risk, regularly use sunscreen with broad spectrum protection and an SPF rating of 15 or higher, along with other sun protection measures including:

- Limit time in the sun, especially between 10am and 2pm.
- Wear long sleeve shirts, pants, hats and sunglasses.
- For children under 6-months, consult a physician.

Other Ingredients:

Aloe Barbadensis Leaf (Aloe Vera Gel) Juice, Aqua, Camellia Sinensis (Green Tea) Extract, Ethylhexylglycerin, Glycerin, Helianthus Annuus (Sunflower) Oil, Lecithin, Octyl Palmitate, Phenoxyethanol, Prunus Amygdalus Dulcis (Sweet Almond) Oil, Sesamum Indicum (Sesame) Seed Oil, Sodium Laurylglucosides Hydroxypropylsulfonate, Theobroma Cacao (Cocoa) Butter, Tocopherol (Vitamin E), Xanthan Gum.